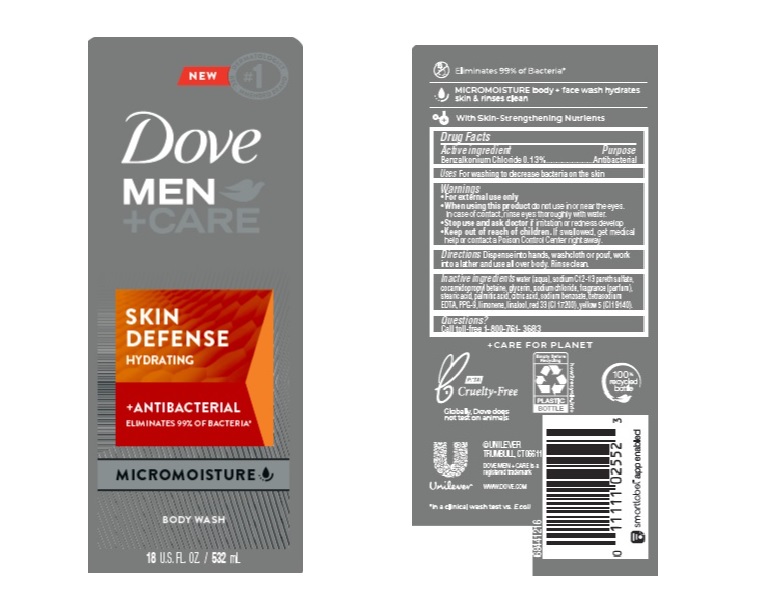 DRUG LABEL: Dove
NDC: 64942-1836 | Form: LIQUID
Manufacturer: Conopco Inc. d/b/a/ Unilever
Category: otc | Type: HUMAN OTC DRUG LABEL
Date: 20241107

ACTIVE INGREDIENTS: BENZALKONIUM CHLORIDE 1.3 mg/1 mL
INACTIVE INGREDIENTS: D&C RED NO. 33; STEARIC ACID; SODIUM CHLORIDE; CITRIC ACID MONOHYDRATE; FD&C YELLOW NO. 5; WATER; GLYCERIN; LIMONENE, (+)-; PALMITIC ACID; EDETATE SODIUM; SODIUM BENZOATE; PPG-9; LINALOOL, (+/-)-; COCAMIDOPROPYL BETAINE

Dove Men +Care Skin Defense Body Wash

DOVE MEN +CARE SKIN DEFENSE BODY WASH - Benzalkonium Chloride

Dove Men +Care Skin Defense Body Wash

Drug Facts

Active ingredient

Benzalkonium Chloride (0.13%)

Purpose

Antibacterial

Uses

For washing to decrease bacteria on the skin

Warnings

• For external use only
• When using this product do not use in or near the eyes. In case of contact, rinse eyes thoroughly with wate r
• Stop use and ask doctor if irritation or redness develop.

• Keep out of reach of children except under adult supervision.

If swallowed, get medical help or contact a poison control Center right away.

Directions

Dispense into hands, wash cloth or pouf, work into lather and use all over body. Rinse clean.

Inactive ingredients

Water (Aqua), Sodium C12-13 Pareth Sulfate, Cocamidopropyl Betaine, Glycerin, Sodium Chloride, Fragrance (Parfum), Stearic Acid, Palmitic Acid, Citric Acid, Sodium Benzoate, Tetrasodium EDTA, PPG-9, Limonene, Linalool, Red 33 (CI 17200), Yellow 5 (CI 19140).

Questions?

Call toll-free 1-800-761-3683